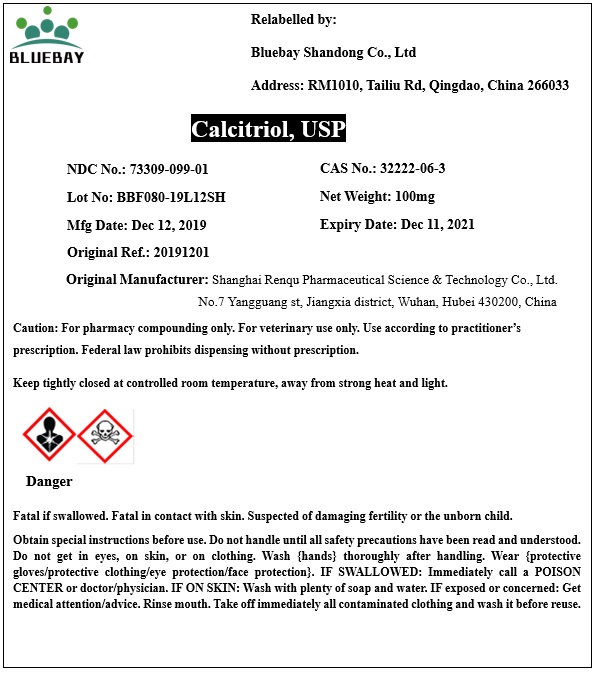 DRUG LABEL: Calcitriol
NDC: 73309-099 | Form: POWDER
Manufacturer: BLUEBAY SHANDONG CO.,LTD
Category: other | Type: BULK INGREDIENT
Date: 20200305

ACTIVE INGREDIENTS: CALCITRIOL 1 mg/1 mg

Calcitriol